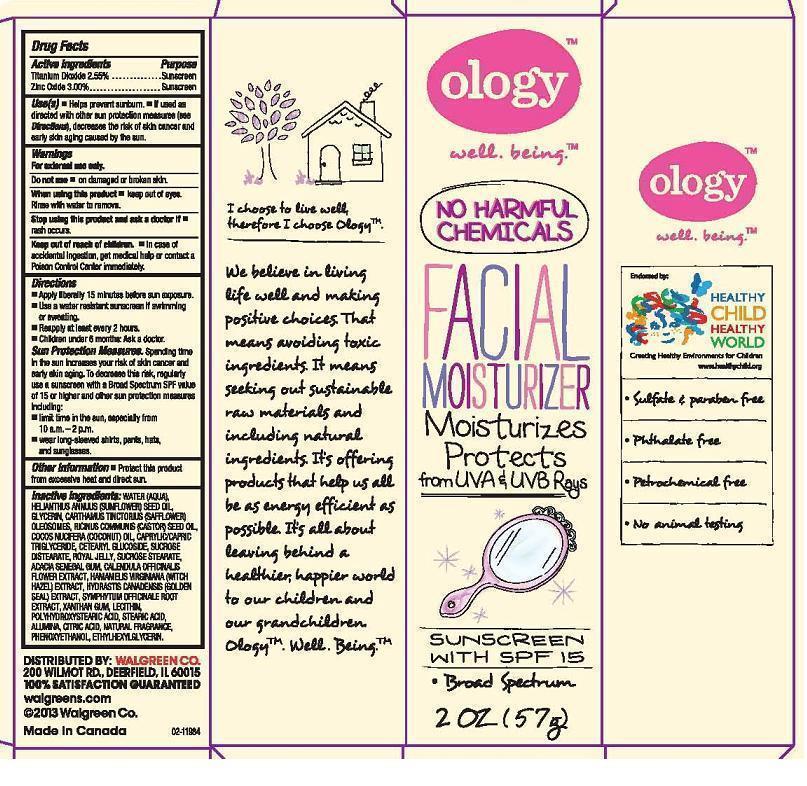 DRUG LABEL: OLOGY
NDC: 0363-3560 | Form: LOTION
Manufacturer: WALGREEN COMPANY
Category: otc | Type: HUMAN OTC DRUG LABEL
Date: 20130408

ACTIVE INGREDIENTS: TITANIUM DIOXIDE 0.0255 g/1 g; ZINC OXIDE 0.03 g/1 g
INACTIVE INGREDIENTS: WATER; SUNFLOWER OIL; GLYCERIN; CARTHAMUS TINCTORIUS SEED OLEOSOMES; CASTOR OIL; COCONUT OIL; MEDIUM-CHAIN TRIGLYCERIDES; CETEARYL GLUCOSIDE; SUCROSE DISTEARATE; ROYAL JELLY; SUCROSE STEARATE; ACACIA; CALENDULA OFFICINALIS FLOWER; HAMAMELIS VIRGINIANA TOP; GOLDENSEAL; COMFREY ROOT; XANTHAN GUM; LECITHIN, SOYBEAN; POLYHYDROXYSTEARIC ACID (2300 MW); STEARIC ACID; ALUMINUM OXIDE; CITRIC ACID MONOHYDRATE; PHENOXYETHANOL; ETHYLHEXYLGLYCERIN

DRUG FACTS

ACTIVE INGREDIENTS

TITANIUM DIOXIDE 2.55%, ZINC OXIDE 3.00%

PURPOSE

SUNSCREEN, SUNSCREEN

USE(S)

HELPS PREVENT SUNBURN. IF USED AS DIRECTED WITH OTHER SUN PROTECION MEASURES (SEE DIRECTIONS), DECREASES THE RISK OF SKIN CANCER AND EARLY SKIN AGING CAUSED BY THE SUN.

WARNINGS

FOR EXTERNAL USE ONLY.

DO NOT USE

ON DAMAGED OR BROKEN SKIN.

WHEN USING THIS PRODUCT

KEEP OUT OF EYES. RINSE WITH WATER TO REMOVE.

STOP USING THIS PRODUCT AND ASK A DOCTOR IF

RASH OCCURS.

KEEP OUT OF REACH OF CHILDREN

IN CASE OF ACCIDENTAL INGESTION, GET MEDICAL HELP OR CONTACT A POISON CONTROL CENTER IMMEDIATELY.

DIRECTIONS

APPLY LIBERALLY 15 MINUTES BEFORE SUN EXPOSURE. USE A WATER RESISTANT SUNSCREEN IF SWIMMING OR SWEATING. REAPPLY AT LEAST EVERY 2 HOURS. CHILDREN UNDER 6 MONTHS: ASK A DOCTOR. SUN PROTECTION MEASURES. SPENDING TIME IN THE SUN INCREASES YOUR RISK OF SKIN CANCER AND EARLY SKIN AGING. TO DECREASE THIS RISK, REGULARLY USE A SUNSCREEN WITH A BROAD SPECTRUM SPF VALUE OF 15 OR HIGHER AND OTHER SUN PROTECTION MEASURES INCLUDING: LIMIT TIME IN THE SUN, ESPECIALLY FROM 10 A.M. - 2 P.M. WEAR LONG-SLEEVED SHIRTS, PANTS, HATS, AND SUNGLASSES.

OTHER INFORMATION

PROTECT THIS PRODUCT FROM EXCESSIVE HEAT AND DIRECT SUN.

INACTIVE INGREDIENTS:

WATER (AQUA), HELIANTHUS ANNUUS (SUNFLOWER) SEED OIL, GLYCERIN, CARTHAMUS TINCTORUS (SAFFLOWER) OLEOSOMES, RICINUS COMMUNIS (CASTOR) SEED OIL, COCOS NUCIFERA (COCONUT) OIL, CAPRYLIC/CAPRIC TRIGLYCERIDE, CETEARYL GLUCOSIDE, SUCROSE DISTEARATE, ROYAL JELLY, SUCROSE STEARATE, ACACIA SENEGAL GUM, CALENDULA OFFICINALIS FLOWER EXTRACT, HAMAMELIS VIRGINIANA (WITCH HAZEL) EXTRACT, HYDRASTIS CANADENSIS (GOLDEN SEAL) EXTRACT, SYMPHYTUM OFFICINALE ROOT EXTRACT, XANTHAN GUM, LECITHIN, POLYHYDROXYSTEARIC ACID, STEARIC ACID, ALUMINA, CITRIC ACID, NATURAL FRAGRANCE, PHENOXYETHANOL, ETHYLHEXYLGLYCERIN.